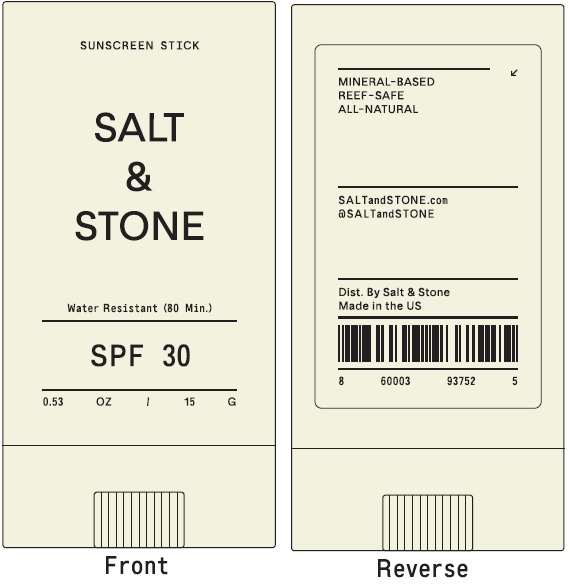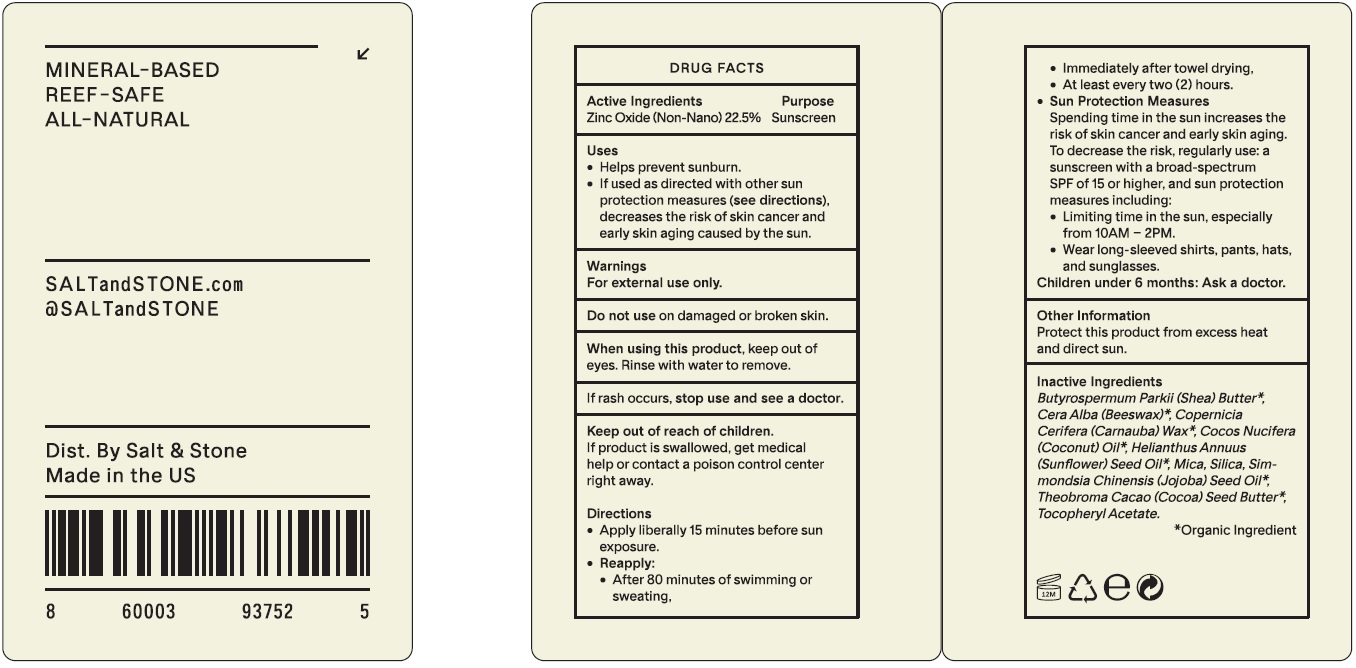 DRUG LABEL: Salt and Stone SPF 30 Sunscreen stick
NDC: 71585-141 | Form: STICK
Manufacturer: Salt and Stone
Category: otc | Type: HUMAN OTC DRUG LABEL
Date: 20231028

ACTIVE INGREDIENTS: ZINC OXIDE 225 mg/1 g
INACTIVE INGREDIENTS: SHEA BUTTER; YELLOW WAX; CARNAUBA WAX; COCONUT OIL; SUNFLOWER OIL; MICA; SILICON DIOXIDE; JOJOBA OIL; COCOA BUTTER; .ALPHA.-TOCOPHEROL ACETATE

Salt & Stone SPF 30 Sunscreen stick

Active Ingredients

Zinc Oxide (Non-Nano) 22.5%

Purpose

Sunscreen

Uses

- Hepls prevent sunburn.
- If used as directed with other sun protection measures (see directions), decreases the risk of skin cancer and early skin aging caused by the sun.

Warnings

For external use only.

Do not use

on damaged or broken skin.

When using this product,

keep out of eyes. Rinse with water to remove.

If rash occurs

Keep out of reach of children.

If product is swallowed, get medical help or contact a poison control center right away.

Directions

- Apply liberally 15 minutes before sun exposure.
- Reapply:
- After 80 minutes of swimming or sweating,
- Immediately after towel drying.
- At least every two (2) hours.
- Spending time in the sun increases the risk of skin cancer and early skin aging. To decrease the risk, regularly use: a suscreen with a broad-spectrum measures including: Sun Protection Measures
- Limiting time in the sun, especially from 10AM - 2PM.
- Wear long-sleeved shirts, pants, hats, and sunglasses.
- Children under 6 months: Ask a doctor.

Other Information

Protect this product from excess heat and direct sun.

Inactive Ingredients

(Shea) Butter, Cera Alba (Beeswax)*, (Carnauba) Wax,* (Coconut) Oil,* (Sunflower) Seed Oil,* Butyrospermum Parkii Copernicia Cerifera Cocos Nucifera Helianthus Annuus Mica, Silica, Simmondsia Chinensis (Jojoba) Seed Oil,* Theobroma Cacao (Cocoa) Seed Butter, Tocopheryl Acetate.

*Organic Ingredient